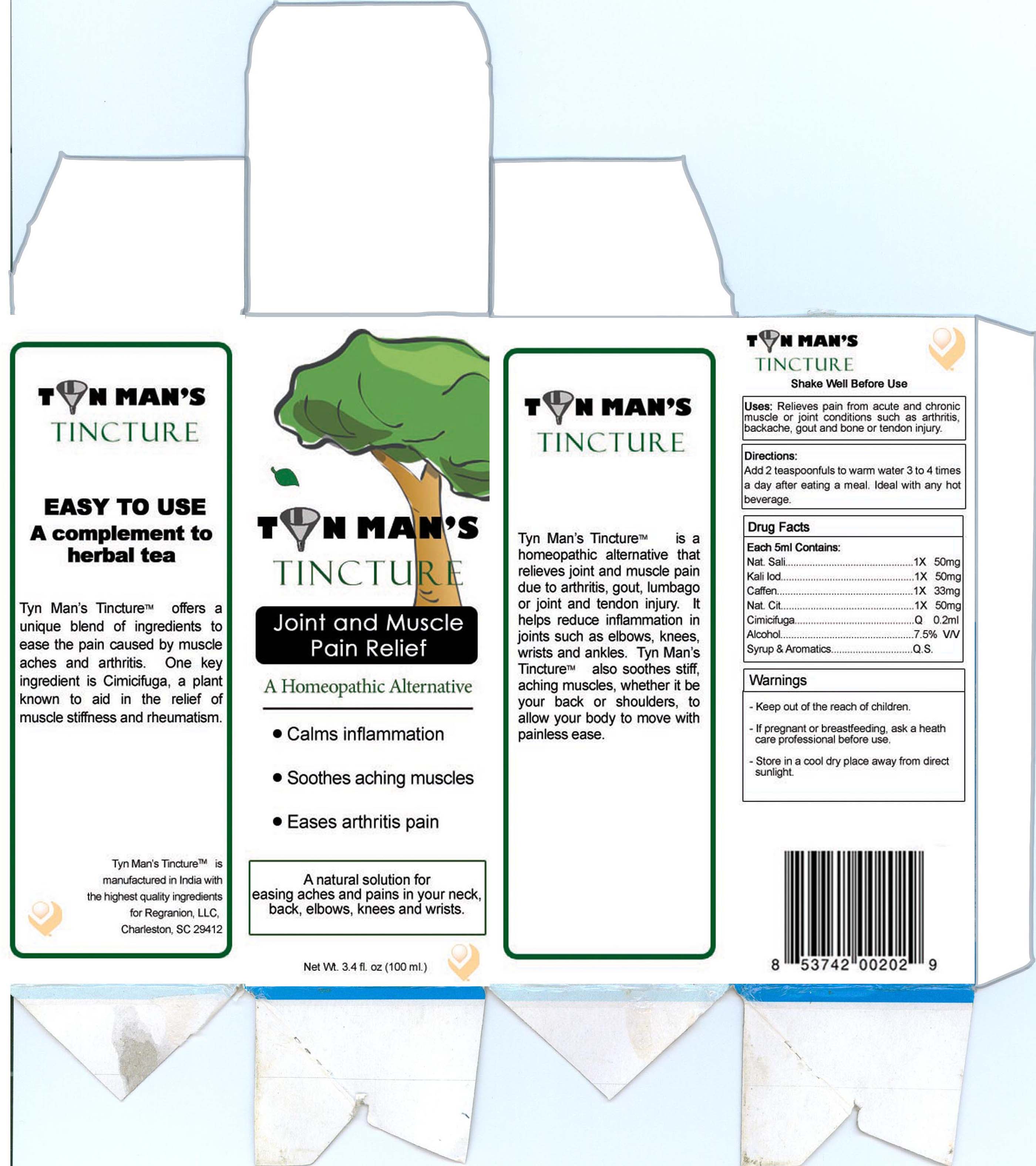 DRUG LABEL: Tyn Mans
NDC: 51720-653 | Form: TINCTURE
Manufacturer: Curative Power Lab PVT LTD
Category: homeopathic | Type: HUMAN OTC DRUG LABEL
Date: 20101029

ACTIVE INGREDIENTS: SODIUM SALICYLATE 1 [hp_X]/100 mL; POTASSIUM IODIDE 1 [hp_X]/100 mL; CAFFEINE 1 [hp_X]/100 mL; SODIUM CITRATE 1 [hp_X]/100 mL; BLACK COHOSH  6 [hp_X]/100 mL
INACTIVE INGREDIENTS: ALCOHOL 1 mL/100 mL

Tyn Man's

ACTIVE INGREDIENT

Nat. Sali. - 1x 50mg
Kali Iod. - 1x 50mg
Caffeine - 1x 33mg
Nat. Cit. - 1x 50mg
Cimicifuga - 0.2ml

INACTIVE INGREDIENT

Alcohol 7.5 percent v/v

Syrup and Aromatics Q.S.

PURPOSE

Tyn Man's is a homeopathic alternative that relieves joint and muscle pain due to arthritis, gout, lumbago, or joint and tendon injury. It helps reduce inflammation in joints such as elbows, knees, wrists, and ankles. Tyn Man's also soothes stiff, aching muscles, whether it be you back or shoulders, to allow your body to move with painless ease.

DESCRIPTION

Tyn Man's. Easy to Use. A complement to herbal tea

Tyn Man's offers a unique blend of ingredients to ease the pain caused by muscle aches and arthritis. One key ingredient is Cimicifuga, a plant known to aid in the relief of muscle stiffness and rheumatism.

INDICATIONS AND USAGE

Tyn Man's. A homeopathic alternative.

- Calms Inflammation
- Soothes aching muscles
- Eases arthritis pain

Uses:

Relieves pain from acute and chronic muscle or joint conditions such as arthritis, backache, gout, and bone or tendon injury.

DOSAGE AND ADMINISTRATION

Add 2 teaspoonfuls to warm water 3 to 4 times a day after eating a meal. Ideal with any warm beverage. Shake well before use.

WARNINGS

- If pregnant or breastfeeding, ask a health care professional before use.

- Store in a cool, dry place away from direct sunlight.

Keep out of the reach of children.